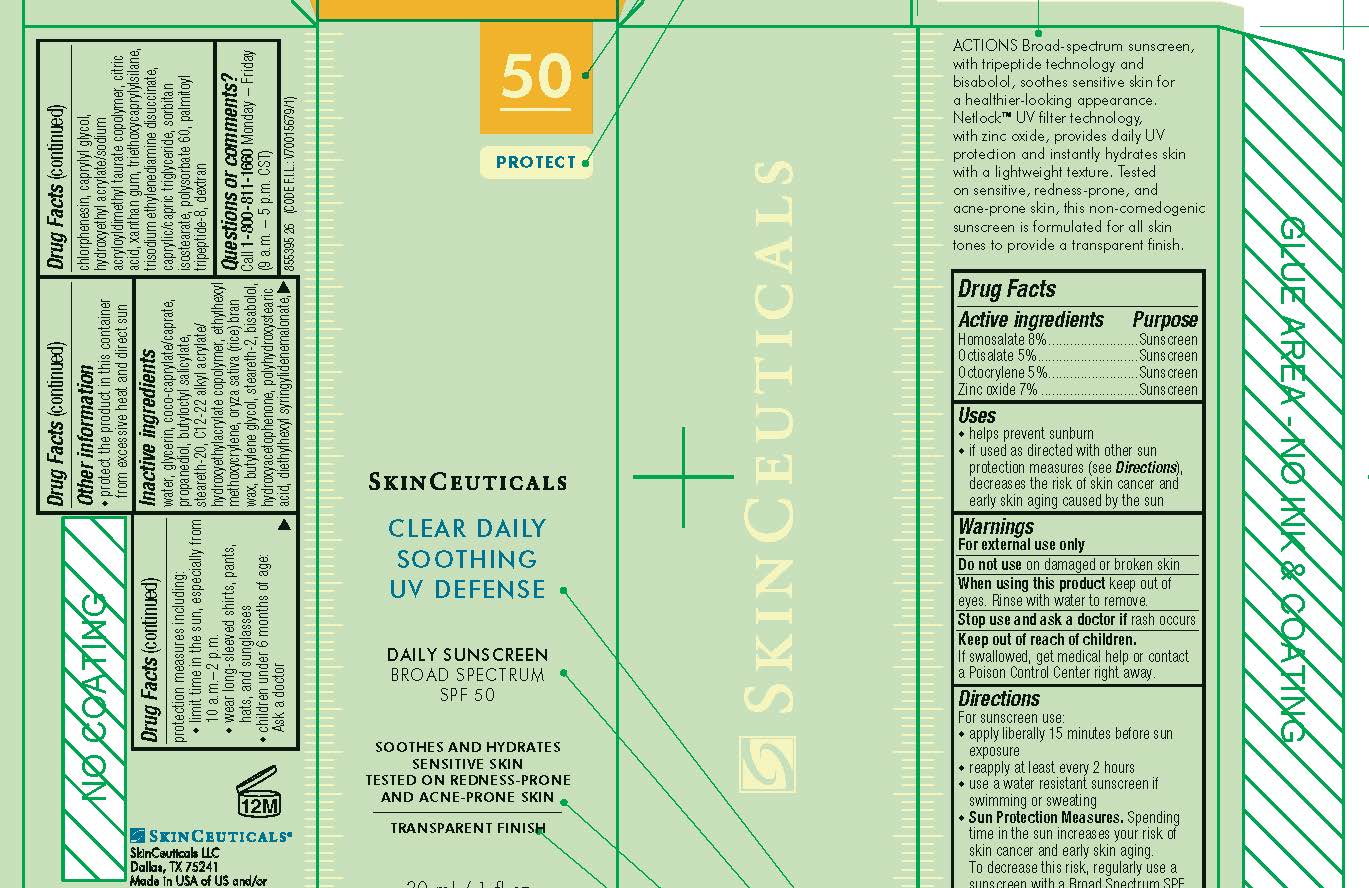 DRUG LABEL: SkinCeuticals Clear Daily Soothing UV Defense Daily Sunscreen Broad Spectrum SPF 50
NDC: 49967-992 | Form: LOTION
Manufacturer: L'Oreal USA Products Inc
Category: otc | Type: HUMAN OTC DRUG LABEL
Date: 20240714

ACTIVE INGREDIENTS: HOMOSALATE 80 mg/1 mL; OCTISALATE 50 mg/1 mL; OCTOCRYLENE 50 mg/1 mL; ZINC OXIDE 70 mg/1 mL
INACTIVE INGREDIENTS: WATER; GLYCERIN; COCO-CAPRYLATE/CAPRATE; PROPANEDIOL; BUTYLOCTYL SALICYLATE; STEARETH-20; ETHYLHEXYL METHOXYCRYLENE; RICE BRAN; BUTYLENE GLYCOL; STEARETH-2; LEVOMENOL; HYDROXYACETOPHENONE; POLYHYDROXYSTEARIC ACID (2300 MW); DIETHYLHEXYL SYRINGYLIDENEMALONATE; CHLORPHENESIN; CAPRYLYL GLYCOL; HYDROXYETHYL ACRYLATE/SODIUM ACRYLOYLDIMETHYL TAURATE COPOLYMER (100000 MPA.S AT 1.5%); CITRIC ACID MONOHYDRATE; XANTHAN GUM; TRIETHOXYCAPRYLYLSILANE; TRISODIUM ETHYLENEDIAMINE DISUCCINATE; MEDIUM-CHAIN TRIGLYCERIDES; SORBITAN ISOSTEARATE; POLYSORBATE 60; PALMITOYL TRIPEPTIDE-8; DEXTRAN 40

Drug Facts

Active ingredients

Homosalate 8%

Octisalate 5%

Octocrylene 5%

Zinc oxide 7%

Purpose

Sunscreen

Uses

- helps prevent sunburn

- if used as directed with other sun protection measures (see Directions), decreases the risk of skin cancer and early skin aging caused by the sun

Warnings

For external use only

Do not use

on damaged or broken skin

When using this product

keep out of eyes. Rinse with water to remove.

Stop use and ask a doctor if

rash occurs

Keep out of reach of children.

If swallowed, get medical help or contact a Poison Control Center right away.

Directions

● apply liberally 15 minutes before sun exposure

● reapply at least every 2 hours

● use a water resistant sunscreen if swimming or sweating

● Sun Protection Measures. Spending time in the sun increases your risk of skin cancer and early skin aging. To decrease this risk,

regularly use a sunscreen with a Broad Spectrum SPF value of 15 or higher and other sun protection measures including:

● limit time in the sun, especially from 10 a.m. – 2 p.m.

● wear long-sleeved shirts, pants, hats, and sunglasses

● children under 6 months of age: Ask a doctor

Other information

protect the product in this container from excessive heat and direct sun

Inactive ingredients

water, glycerin, coco-caprylate/caprate, propanediol, butyloctyl salicylate, steareth-20, c12-22 alkyl acrylate/hydroxyethylacrylate copolymer, ethylhexyl methoxycrylene, oryza sativa (rice) bran wax, butylene glycol, steareth-2, bisabolol, hydroxyacetophenone, polyhydroxystearic acid, diethylhexyl syringylidenemalonate, chlorphenesin, caprylyl glycol, hydroxyethyl acrylate/sodium acryloyldimethyl taurate copolymer, citric acid, xanthan gum, triethoxycaprylylsilane, trisodium ethylenediamine disuccinate, caprylic/capric triglyceride, sorbitan isostearate, polysorbate 60, palmitoyl tripeptide-8, dextran

Questions or comments?

Call 1-800-811-1660

Monday - Friday (9 a.m. - 5 p.m. CST)